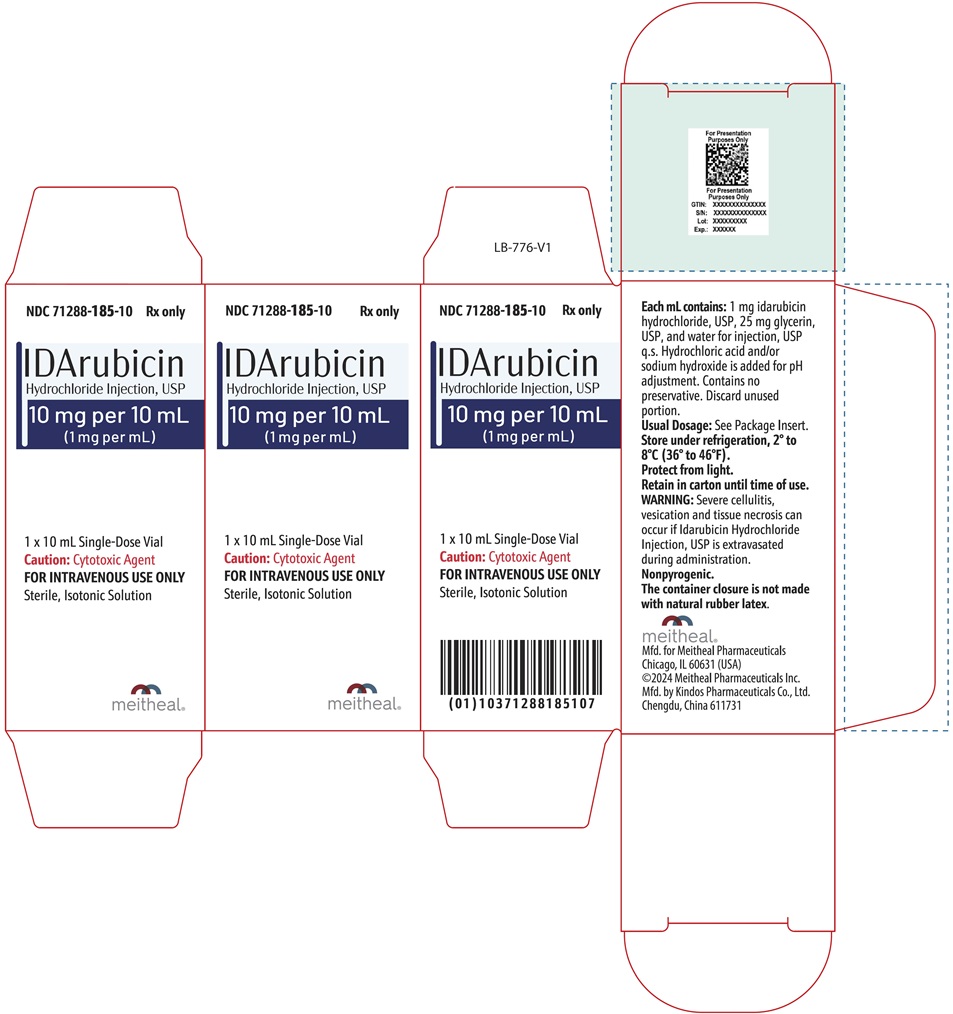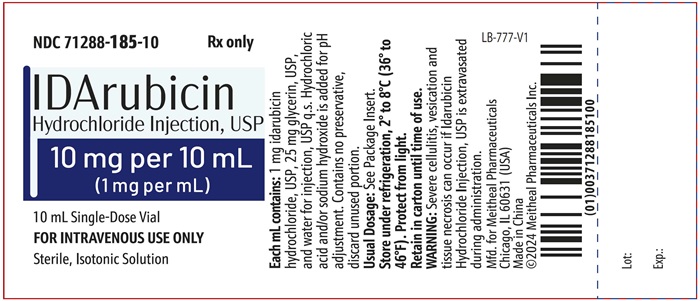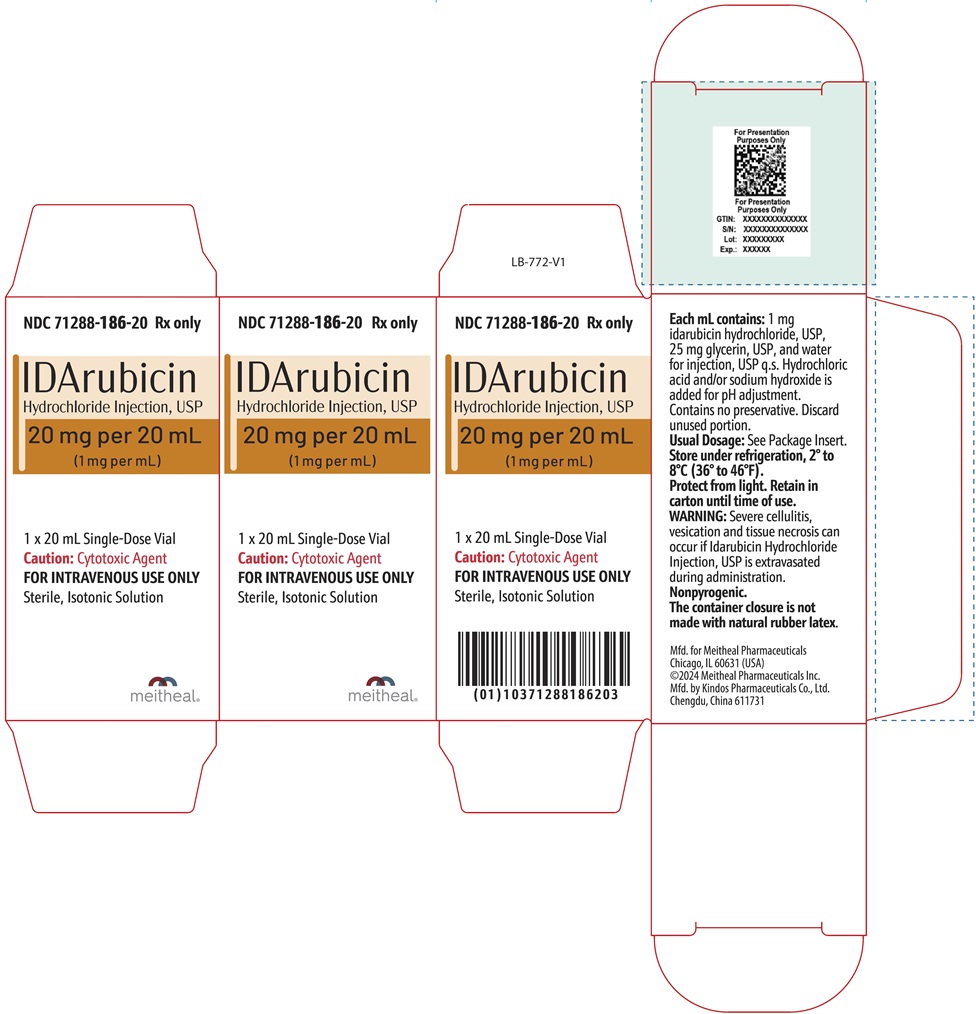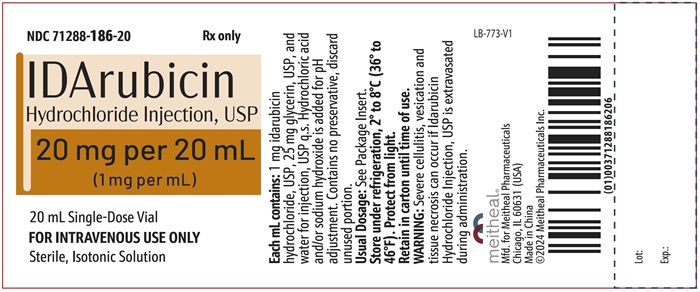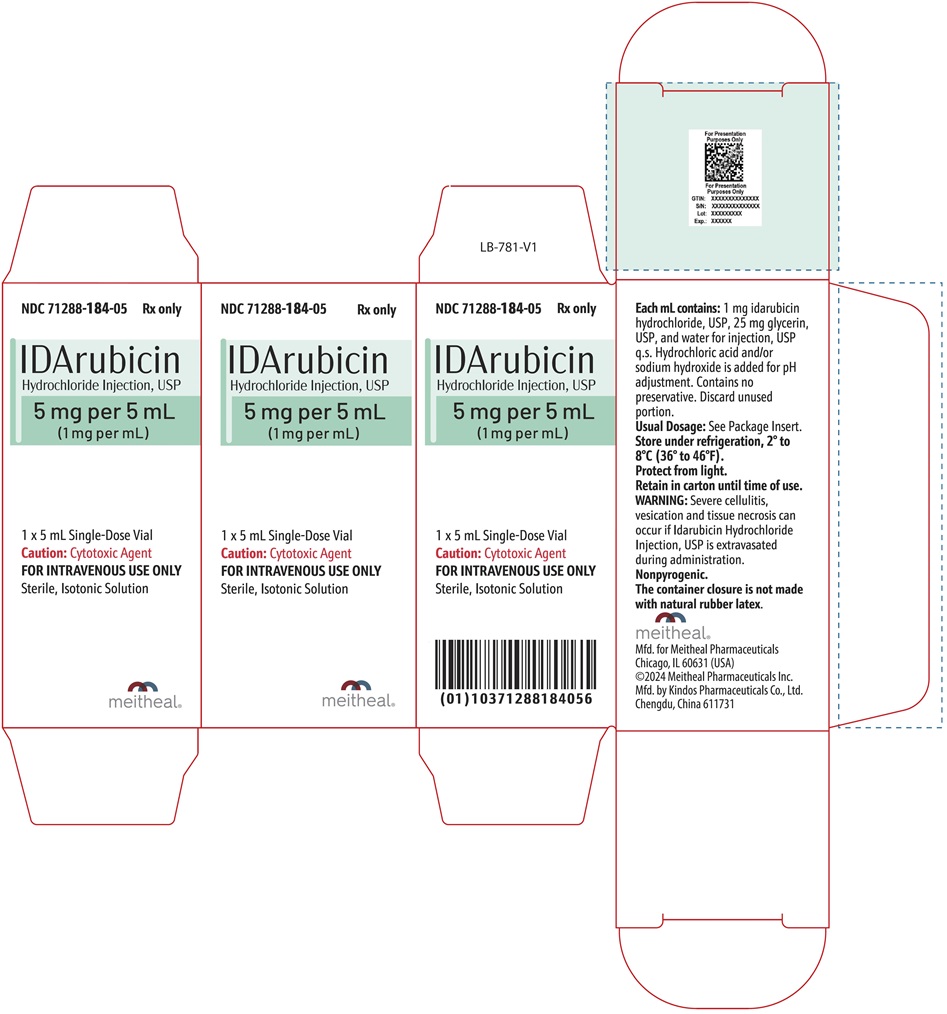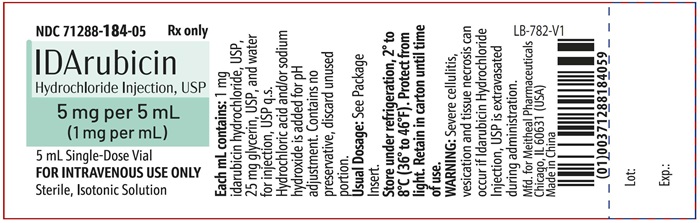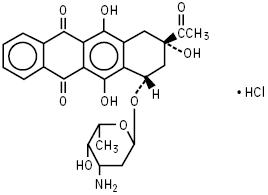 DRUG LABEL: Idarubicin Hydrochloride
NDC: 71288-184 | Form: INJECTION, SOLUTION
Manufacturer: Meitheal Pharmaceuticals Inc.
Category: prescription | Type: HUMAN PRESCRIPTION DRUG LABEL
Date: 20250509

ACTIVE INGREDIENTS: IDARUBICIN HYDROCHLORIDE 1 mg/1 mL
INACTIVE INGREDIENTS: GLYCERIN; WATER

IDArubicin
Hydrochloride Injection, USP
For Intravenous Use Only
meitheal®
Rx Only

WARNINGS

1. Idarubicin Hydrochloride Injection should be given slowly into a freely flowing intravenous infusion. It must never be given intramuscularly or subcutaneously. Severe local tissue necrosis can occur if there is extravasation during administration.

2. As is the case with other anthracyclines the use of Idarubicin Hydrochloride Injection can cause myocardial toxicity leading to congestive heart failure. Cardiac toxicity is more common in patients who have received prior anthracyclines or who have pre-existing cardiac disease.

3. As is usual with antileukemic agents, severe myelosuppression occurs when Idarubicin Hydrochloride Injection is used at effective therapeutic doses.

4. It is recommended that Idarubicin Hydrochloride Injection be administered only under the supervision of a physician who is experienced in leukemia chemotherapy and in facilities with laboratory and supportive resources adequate to monitor drug tolerance and protect and maintain a patient compromised by drug toxicity. The physician and institution must be capable of responding rapidly and completely to severe hemorrhagic conditions and/or overwhelming infection.

5. Dosage should be reduced in patients with impaired hepatic or renal function (see DOSAGE AND ADMINISTRATION).

DESCRIPTION

Idarubicin Hydrochloride Injection, USP contains idarubicin hydrochloride, USP and is a sterile, semi-synthetic, preservative-free solution (PFS) antineoplastic anthracycline for intravenous use. Chemically, idarubicin hydrochloride, USP is 5, 12-Naphthacenedione, 9-acetyl-7-[(3-amino-2,3,6-trideoxy-α-L-lyxo-hexopyranosyl)oxy]-7,8,9,10-tetrahydro-6,9,11-trihydroxyhydrochloride, (7S-cis). The structural formula is as follows:

C26H27NO9•HCl M.W. 533.95

Idarubicin Hydrochloride Injection, USP is a sterile, clear, orange-red, isotonic parenteral preservative-free solution, available in 5 mL (5 mg), 10 mL (10 mg) and 20 mL (20 mg) single-dose-only vials.

Each mL contains idarubicin hydrochloride USP, 1 mg (equivalent to 0.93 mg idarubicin free base) and the following inactive ingredients: glycerin USP, 25 mg and q.s. water for injection, USP. Hydrochloric acid and/or sodium hydroxide is used to adjust pH to a target of 3.5.

CLINICAL PHARMACOLOGY

Mechanism of Action

Idarubicin hydrochloride is a DNA-intercalating analog of daunorubicin which has an inhibitory effect on nucleic acid synthesis and interacts with the enzyme topoisomerase II. The absence of a methoxy group at position 4 of the anthracycline structure gives the compound a high lipophilicity which results in an increased rate of cellular uptake compared with other anthracyclines.

Pharmacokinetics

General Pharmacokinetics

Pharmacokinetic studies have been performed in adult leukemia patients with normal renal and hepatic function following intravenous administration of 10 to 12 mg/m^2 of idarubicin daily for 3 to 4 days as a single agent or combined with cytarabine. The plasma concentrations of idarubicin are best described by a two or three compartment open model. The elimination rate of idarubicin from plasma is slow with an estimated mean terminal half-life of 22 hours (range, 4 to 48 hours) when used as a single agent and 20 hours (range, 7 to 38 hours) when used in combination with cytarabine. The elimination of the primary active metabolite, idarubicinol, is considerably slower than that of the parent drug with an estimated mean terminal half-life that exceeds 45 hours; hence, its plasma levels are sustained for a period greater than 8 days.

Distribution

The disposition profile shows a rapid distributive phase with a very high volume of distribution presumably reflecting extensive tissue binding. Studies of cellular (nucleated blood and bone marrow cells) drug concentrations in leukemia patients have shown that peak cellular idarubicin concentrations are reached a few minutes after injection. Concentrations of idarubicin and idarubicinol in nucleated blood and bone marrow cells are more than a hundred times the plasma concentrations. Idarubicin disappearance rates in plasma and cells were comparable with a terminal half-life of about 15 hours. The terminal half-life of idarubicinol in cells was about 72 hours. The extent of drug and metabolite accumulation predicted in leukemia patients for Days 2 and 3 of dosing, based on the mean plasma levels and half-life obtained after the first dose, is 1.7- and 2.3-fold, respectively, and suggests no change in kinetics following a daily × 3 regimen. The percentages of idarubicin and idarubicinol bound to human plasma proteins averaged 97% and 94%, respectively, at concentrations similar to maximum plasma levels obtained in the pharmacokinetic studies. The binding is concentration independent. The plasma clearance is twice the expected hepatic plasma flow indicating extensive extrahepatic metabolism.

Metabolism

The primary active metabolite formed is idarubicinol. As idarubicinol has cytotoxic activity, it presumably contributes to the effects of idarubicin.

Elimination

The drug is eliminated predominately by biliary and to a lesser extent by renal excretion, mostly in the form of idarubicinol.

Pharmacokinetics in Special Populations

Pediatric Patients

Idarubicin studies in pediatric leukemia patients, at doses of 4.2 to 13.3 mg/m^2/day × 3, suggest dose independent kinetics. There is no difference between the half-lives of the drug following daily × 3 or weekly × 3 administration. Cerebrospinal fluid (CSF) levels of idarubicin and idarubicinol were measured in pediatric leukemia patients treated intravenously. Idarubicin was detected in 2 of 21 CSF samples (0.14 and 1.57 ng/mL), while idarubicinol was detected in 20 of these 21 CSF samples obtained 18 to 30 hours after dosing (mean = 0.51 ng/mL; range, 0.22 to 1.05 ng/mL). The clinical relevance of these findings is unknown.

Hepatic and Renal Impairment

The pharmacokinetics of idarubicin have not been evaluated in leukemia patients with hepatic impairment. It is expected that in patients with moderate or severe hepatic dysfunction, the metabolism of idarubicin may be impaired and lead to higher systemic drug levels. The disposition of idarubicin may be also affected by renal impairment. Therefore, a dose reduction should be considered in patients with hepatic and/or renal impairment (see DOSAGE AND ADMINISTRATION).

Drug-Drug Interactions

No formal drug interaction studies have been performed.

CLINICAL STUDIES

Four prospective randomized studies, three U.S. and one Italian, have been conducted to compare the efficacy and safety of idarubicin (IDR) to that of daunorubicin (DNR), each in combination with cytarabine as induction therapy in previously untreated adult patients with acute myeloid leukemia (AML). These data are summarized in the following table and demonstrate significantly greater complete remission rates for the IDR regimen in two of the three U.S. studies and significantly longer overall survival for the IDR regimen in two of the three U.S. studies.

 | Inductiona Regimen Dose in mg/m^2 -Daily x 3 Days |  | Complete Remission Rate, All Pts Randomized |  | Median Survival (Days) All Pts Randomized
 | IDR | DNR | IDR | DNR | IDR | DNR
U.S. (IND Studies)
1. MSKCC | 12b | 50b | 51/65* | 38/65 | 508* | 435
(Age ≤ 60 years) |  |  | (78%) | (58%)
2. SEG | 12c | 45c | 76/111* | 65/119 | 328 | 277
(Age ≥ 15 years) |  |  | (69%) | (55%)
3. U.S. Multicenter | 13c | 45c | 68/101 | 66/113 | 393* | 281
(Age ≥ 18 years) |  |  | (67%) | (58%)
Foreign (non-IND study)
GIMEMA | 12c | 45c | 49/124 | 49/125 | 87 | 169
(Age ≥ 55 years) |  |  | (40%) | (39%)

*Overall p < 0.05, unadjusted for prognostic factors or multiple endpoints

Abbreviations: MSKCC=Memorial Sloan Kettering Cancer Center; SEG= Southeastern Cancer Study Group; GIMEMA= Gruppo Italiano Malattie Ematologiche Maligne dell' Adulto; IDR=Idarubicin; DNR=Daunorubicin; Pts=Patients; IND=Investigational New Drug

aPatients who had persistent leukemia after the first induction course received a second course

bCytarabine 25 mg/m^2 bolus IV followed by 200 mg/m^2 daily x 5 days by continuous infusion

cCytarabine 100 mg/m^2 daily x 7 days by continuous infusion

There is no consensus regarding optional regimens to be used for consolidation; however, the following consolidation regimens were used in U.S. controlled trials. Patients received the same anthracycline for consolidation as was used for induction.

Studies 1 and 3 utilized 2 courses of consolidation therapy consisting of idarubicin 12 or 13 mg/m^2 daily for 2 days, respectively (or DNR 50 or 45 mg/m^2 daily for 2 days), and cytarabine, either 25 mg/m^2 by IV bolus followed by 200 mg/m^2 daily by continuous infusion for 4 days (Study 1), or 100 mg/m^2 daily for 5 days by continuous infusion (Study 3). A rest period of 4 to 6 weeks is recommended prior to initiation of consolidation and between the courses. Hematologic recovery is mandatory prior to initiation of each consolidation course.

Study 2 utilized 3 consolidation courses, administered at intervals of 21 days or upon hematologic recovery. Each course consisted of idarubicin 15 mg/m^2 IV for 1 dose (or DNR 50 mg/m^2 IV for 1 dose), cytarabine 100 mg/m^2 every 12 hours for 10 doses and 6-thioguanine 100 mg/m^2 orally for 10 doses. If severe myelosuppression occurred, subsequent courses were given with 25% reduction in the doses of all drugs. In addition, this study included 4 courses of maintenance therapy (2 days of the same anthracycline as was used in induction and 5 days of cytarabine).

Toxicities and duration of aplasia were similar during induction on the 2 arms in the U.S. studies except for an increase in mucositis on the IDR arm in one study. During consolidation, duration of aplasia on the IDR arm was longer in all three studies and mucositis was more frequent in two studies. During consolidation, transfusion requirements were higher on the IDR arm in the two studies in which they were tabulated, and patients on the IDR arm in Study 3 spent more days on IV antibiotics (Study 3 used a higher dose of idarubicin).

The benefit of consolidation and maintenance therapy in prolonging the duration of remission and survival is not proven.

Intensive maintenance with idarubicin is not recommended in view of the considerable toxicity (including deaths in remission) experienced by patients during the maintenance phase of Study 2.

A higher induction death rate was noted in patients on the IDR arm in the Italian trial. Since this was not noted in patients of similar age in the U.S. trials, one may speculate that it was due to a difference in the level of supportive care.

INDICATIONS AND USAGE

Idarubicin Hydrochloride Injection in combination with other approved antileukemic drugs is indicated for the treatment of acute myeloid leukemia (AML) in adults. This includes French-American-British (FAB) classifications M1 through M7.

WARNINGS

Idarubicin is intended for administration under the supervision of a physician who is experienced in leukemia chemotherapy.

Idarubicin is a potent bone marrow suppressant. Idarubicin should not be given to patients with pre-existing bone marrow suppression induced by previous drug therapy or radiotherapy unless the benefit warrants the risk.

Severe myelosuppression will occur in all patients given a therapeutic dose of this agent for induction, consolidation or maintenance. Careful hematologic monitoring is required. Deaths due to infection and/or bleeding have been reported during the period of severe myelosuppression. Facilities with laboratory and supportive resources adequate to monitor drug tolerability and protect and maintain a patient compromised by drug toxicity should be available. It must be possible to treat rapidly and completely a severe hemorrhagic condition and/or a severe infection.

Pre-existing heart disease and previous therapy with anthracyclines at high cumulative doses or other potentially cardiotoxic agents are co-factors for increased risk of idarubicin-induced cardiac toxicity and the benefit to risk ratio of idarubicin therapy in such patients should be weighed before starting treatment with idarubicin.

Myocardial toxicity as manifested by potentially fatal congestive heart failure, acute life-threatening arrhythmias or other cardiomyopathies may occur following therapy with idarubicin. Appropriate therapeutic measures for the management of congestive heart failure and/or arrhythmias are indicated.

Cardiac function should be carefully monitored during treatment in order to minimize the risk of cardiac toxicity of the type described for other anthracycline compounds. The risk of such myocardial toxicity may be higher following concomitant or previous radiation to the mediastinal-pericardial area or in patients with anemia, bone marrow depression, infections, leukemic pericarditis and/or myocarditis, active or dormant cardiovascular disease, previous therapy with other anthracyclines or anthracenediones, and concomitant use of drugs with the ability to suppress cardiac contractility or cardiotoxic drugs (e.g., trastuzumab, cyclophosphamide and paclitaxel). Due to the increased risk of cardiotoxicity, avoid concomitant use of Idarubicin Hydrochloride Injection until the cardiotoxic agent has been discontinued for at least 5 half-lives, and specifically avoid Idarubicin Hydrochloride Injection for up to 7 months after stopping trastuzumab.

While there are no reliable means for predicting congestive heart failure, cardiomyopathy induced by anthracyclines is usually associated with a decrease of the left ventricular ejection fraction (LVEF) from pretreatment baseline values.

Since hepatic and/or renal function impairment can affect the disposition of idarubicin, liver and kidney function should be evaluated with conventional clinical laboratory tests (using serum bilirubin and serum creatinine as indicators) prior to and during treatment. In a number of Phase III clinical trials, treatment was not given if bilirubin and/or creatinine serum levels exceeded 2 mg%. However, in one Phase III trial, patients with bilirubin levels between 2.6 and 5 mg% received the anthracycline with a 50% reduction in dose. Dose reduction of idarubicin should be considered if the bilirubin and/or creatinine levels are above the normal range (see DOSAGE AND ADMINISTRATION).

Pregnancy

Idarubicin was embryotoxic and teratogenic in the rat at a dose of 1.2 mg/m^2/day or one tenth the human dose, which was nontoxic to dams. Idarubicin was embryotoxic but not teratogenic in the rabbit even at a dose of 2.4 mg/m^2/day or two tenths the human dose, which was toxic to dams. There is no conclusive information about idarubicin adversely affecting human fertility or causing teratogenesis. There has been one report of a fetal fatality after maternal exposure to idarubicin during the second trimester.

There are no adequate and well-controlled studies in pregnant women. Idarubicin Hydrochloride Injection should be used during pregnancy only if the potential benefit justifies the potential risk to the fetus. If Idarubicin Hydrochloride Injection is to be used during pregnancy, or if the patient becomes pregnant during therapy, the patient should be apprised and informed of the potential hazard to the fetus. Women of childbearing potential should be advised to avoid pregnancy. Women of childbearing potential should be advised to use effective contraception during treatment with Idarubicin Hydrochloride Injection and for 6.5 months after the last dose. Men with female partners of childbearing potential should be advised to use effective contraception during treatment with Idarubicin Hydrochloride Injection and for 3.5 months after the last dose. Both men and women should seek advice for fertility preservation before treatment and/or seek genetic counselling after treatment.

PRECAUTIONS

General

Therapy with idarubicin requires close observation of the patient and careful laboratory monitoring. Hyperuricemia secondary to rapid lysis of leukemic cells may be induced. Appropriate measures must be taken to prevent hyperuricemia and to control any systemic infection before beginning therapy.

Extravasation of idarubicin can cause severe local tissue necrosis. Extravasation may occur with or without an accompanying stinging or burning sensation even if blood returns well on aspiration of the infusion needle. If signs or symptoms of extravasation occur the injection or infusion should be terminated immediately and restarted in another vein (see DOSAGE AND ADMINISTRATION).

Laboratory Tests

Frequent complete blood counts and monitoring of hepatic and renal function tests are recommended.

Carcinogenesis, Mutagenesis, Impairment of Fertility

Formal long-term carcinogenicity studies have not been conducted with idarubicin. Idarubicin and related compounds have been shown to have mutagenic and carcinogenic properties when tested in experimental models (including bacterial systems, mammalian cells in culture and female Sprague-Dawley rats).

In male dogs given 1.8 mg/m^2/day 3 times/week (about one seventh the weekly human dose on a mg/m^2 basis) for 13 weeks, or 3 times the human dose, testicular atrophy was observed with inhibition of spermatogenesis and sperm maturation with few or no mature sperm. These effects were not readily reversed after a recovery of 8 weeks.

Pregnancy

(See WARNINGS).

Nursing Mothers

It is not known whether this drug is excreted in human milk. Because many drugs are excreted in human milk and because of the potential for serious adverse reactions in nursing infants from idarubicin, mothers should discontinue nursing prior to taking this drug and do not breastfeed during treatment and for 14 days after
last dose.

Pediatric Use

Safety and effectiveness in children have not been established.

Geriatric Use

Patients over 60 years of age who were undergoing induction therapy experienced congestive heart failure, serious arrhythmias, chest pain, myocardial infarction, and asymptomatic declines in LVEF more frequently than younger patients (see ADVERSE REACTIONS).

ADVERSE REACTIONS

Approximately 550 patients with AML have received idarubicin in combination with cytarabine in controlled clinical trials worldwide. In addition, over 550 patients with acute leukemia have been treated in uncontrolled trials utilizing idarubicin as a single agent or in combination. The table below lists the adverse experiences reported in U.S. Study 2 (see CLINICAL STUDIES) and is representative of the experiences in other studies. These adverse experiences constitute all reported or observed experiences, including those not considered to be drug related. Patients undergoing induction therapy for AML are seriously ill due to their disease, are receiving multiple transfusions, and concomitant medications including potentially toxic antibiotics and antifungal agents. The contribution of the study drug to the adverse experience profile is difficult to establish.

Induction Phase | Percentage of Patients
Adverse Experiences | IDR; (N=110) | DNR; (N=118)
Infection | 95% | 97%
Nausea & Vomiting | 82% | 80%
Hair Loss | 77% | 72%
Abdominal Cramps/Diarrhea | 73% | 68%
Hemorrhage | 63% | 65%
Mucositis | 50% | 55%
Dermatologic | 46% | 40%
Mental Status | 41% | 34%
Pulmonary-Clinical | 39% | 39%
Fever (not elsewhere classified) | 26% | 28%
Headache | 20% | 24%
Cardiac-Clinical | 16% | 24%
Neurologic-Peripheral Nerves | 7% | 9%
Pulmonary Allergy | 2% | 4%
Seizure | 4% | 5%
Cerebellar | 4% | 4%

Abbreviations: IDR=Idarubicin; DNR=Daunorubicin

The duration of aplasia and incidence of mucositis were greater on the IDR arm than the DNR arm, especially during consolidation in some U.S. controlled trials (see CLINICAL STUDIES).

The following information reflects experience based on U.S. controlled clinical trials.

Myelosuppression

Severe myelosuppression is the major toxicity associated with idarubicin therapy, but this effect of the drug is required in order to eradicate the leukemic clone. During the period of myelosuppression, patients are at risk of developing infection and bleeding which may be life-threatening or fatal.

Gastrointestinal

Nausea and/or vomiting, mucositis, abdominal pain and diarrhea were reported frequently, but were severe (equivalent to WHO Grade 4) in less than 5% of patients. Severe enterocolitis with perforation has been reported rarely. The risk of perforation may be increased by instrumental intervention. The possibility of perforation should be considered in patients who develop severe abdominal pain and appropriate steps for diagnosis and management should be taken.

Dermatologic

Alopecia was reported frequently and dermatologic reactions including generalized rash, urticaria and a bullous erythrodermatous rash of the palms and soles have occurred. The dermatologic reactions were usually attributed to concomitant antibiotic therapy. Local reactions including hives at the injection site have been reported. Recall of skin reaction due to prior radiotherapy has occurred with idarubicin administration.

Hepatic and Renal

Changes in hepatic and renal function tests have been observed. These changes were usually transient and occurred in the setting of sepsis and while patients were receiving potentially hepatotoxic and nephrotoxic antibiotics and antifungal agents. Severe changes in renal function (equivalent to WHO Grade 4) occurred in no more than 1% of patients, while severe changes in hepatic function (equivalent to WHO Grade 4) occurred in less than 5% of patients.

Cardiac

Congestive heart failure (frequently attributed to fluid overload), serious arrhythmias including atrial fibrillation, chest pain, myocardial infarction and asymptomatic declines in LVEF have been reported in patients undergoing induction therapy for AML. Myocardial insufficiency and arrhythmias were usually reversible and occurred in the setting of sepsis, anemia and aggressive intravenous fluid administration. The events were reported more frequently in patients over age 60 years and in those with pre-existing cardiac disease.

To report SUSPECTED ADVERSE REACTIONS, contact Meitheal Pharmaceuticals, Inc. at 1-844-824-8426 or FDA at 1-800-FDA-1088 or www.fda.gov/medwatch.

OVERDOSAGE

There is no known antidote to idarubicin. Two cases of fatal overdosage in patients receiving therapy for AML have been reported. The doses were 135 mg/m^2 over 3 days and 45 mg/m^2 of idarubicin and 90 mg/m^2 of daunorubicin over a three day period.

It is anticipated that overdosage with idarubicin will result in severe and prolonged myelosuppression and possibly in increased severity of gastrointestinal toxicity. Adequate supportive care including platelet transfusions, antibiotics and symptomatic treatment of mucositis is required. The effect of acute overdose on cardiac function is not fully known, but severe arrhythmia occurred in 1 of the 2 patients exposed. It is anticipated that very high doses of idarubicin may cause acute cardiac toxicity and may be associated with a higher incidence of delayed cardiac failure.

Disposition studies with idarubicin in patients undergoing dialysis have not been carried out. The profound multicompartment behavior, extensive extravascular distribution and tissue binding, coupled with the low unbound fraction available in the plasma pool make it unlikely that therapeutic efficacy or toxicity would be altered by conventional peritoneal or hemodialysis.

DOSAGE AND ADMINISTRATION

(SeeWARNINGS)

For induction therapy in adult patients with AML the following dose schedule is recommended:

Idarubicin Hydrochloride Injection 12 mg/m^2 daily for 3 days by slow (10 to 15 min) intravenous injection in combination with cytarabine. The cytarabine may be given as 100 mg/m^2 daily by continuous infusion for 7 days or as cytarabine 25 mg/m^2 intravenous bolus followed by cytarabine 200 mg/m^2 daily for 5 days continuous infusion. In patients with unequivocal evidence of leukemia after the first induction course, a second course may be administered. Administration of the second course should be delayed in patients who experience severe mucositis, until recovery from this toxicity has occurred, and a dose reduction of 25% is recommended. In patients with hepatic and/or renal impairment, a dose reduction of Idarubicin Hydrochloride Injection should be considered. Idarubicin Hydrochloride Injection should not be administered if the bilirubin level exceeds 5 mg% (see WARNINGS).

The benefit of consolidation in prolonging the duration of remissions and survival is not proven. There is no consensus regarding optional regimens to be used for consolidation (see CLINICAL STUDIES for doses used in U.S. Clinical studies).

Preparation and Administration Precautions

Caution in handling the solution must be exercised as skin reactions associated with Idarubicin Hydrochloride Injection may occur. Skin accidentally exposed to Idarubicin Hydrochloride Injection should be washed thoroughly with soap and water and if the eyes are involved, standard irrigation techniques should be used immediately. The use of goggles, gloves, and protective gowns is recommended during preparation and administration of the drug.

Care in the administration of Idarubicin Hydrochloride Injection will reduce the chance of perivenous infiltration. It may also decrease the chance of local reactions such as urticaria and erythematous streaking. During intravenous administration of Idarubicin Hydrochloride Injection extravasation may occur with or without an accompanying stinging or burning sensation even if blood returns well on aspiration of the infusion needle. If any signs or symptoms of extravasation have occurred, the injection or infusion should be immediately terminated and restarted in another vein. If it is known or suspected that subcutaneous extravasation has occurred, it is recommended that intermittent ice packs (1/2 hour immediately, then 1/2 hour 4 times per day for 3 days) be placed over the area of extravasation and that the affected extremity be elevated. Because of the progressive nature of extravasation reactions, the area of injection should be frequently examined and plastic surgery consultation obtained early if there is any sign of a local reaction such as pain, erythema, edema or vesication. If ulceration begins or there is severe persistent pain at the site of extravasation, early wide excision of the involved area should be considered.

Idarubicin Hydrochloride Injection should be administered slowly (over 10 to 15 minutes) into the tubing of a freely running intravenous infusion of Sodium Chloride Injection, USP (0.9%) or 5% Dextrose Injection, USP. The tubing should be attached to a Butterfly needle or other suitable device and inserted preferably into a large vein. Idarubicin Hydrochloride Injection is provided in single dose vials. Discard unused portion.

Incompatibility

Unless specific compatibility data are available, Idarubicin Hydrochloride Injection should not be mixed with other drugs. Precipitation occurs with heparin. Prolonged contact with any solution of an alkaline pH will result in degradation of the drug.

Parenteral drug products should be inspected visually for particulate matter and discoloration prior to administration whenever solution and containers permit.

Handling and Disposal

Procedures for handling and disposal of anticancer drugs should be considered. Several guidelines on this subject have been published.^1–8 There is no general agreement that all of the procedures recommended in the guidelines are necessary or appropriate.

HOW SUPPLIED

Idarubicin Hydrochloride Injection, USP is a clear, orange-red, isotonic parenteral solution, free from visible particles for intravenous use only and is available as below:

NDC | Idarubicin Hydrochloride Injection, USP (1 mg per mL) | Package Factor
71288-184-05 | 5 mg per 5 mL Single-Dose Vial | 1 vial per carton
71288-185-10 | 10 mg per 10 mL Single-Dose Vial | 1 vial per carton
71288-186-20 | 20 mg per 20 mL Single-Dose Vial | 1 vial per carton

Contains no preservative. Discard unused portion.

Sterile, Nonpyrogenic.

The container closure is not made with natural rubber latex.

Store under refrigeration 2° to 8°C (36° to 46°F). Protect from light. Retain in carton until time of use.

REFERENCES

1. ONS Clinical Practice Committee. Cancer Chemotherapy Guidelines and Recommendations for Practice. Pittsburgh, PA: Oncology Nursing Society. 1999: 32-41.
2. Recommendations for the Safe Handling of Parenteral Antineoplastic Drugs. Washington, DC; Division of Safety, Clinical Center Pharmacy Department and Cancer Nursing Services, National Institutes of Health; 1992. US Department of Health and Human Services, Public Health Service Publication NIH 92-2621.
3. AMA Council on Scientific Affairs. Guidelines for Handling Parenteral Antineoplastics. JAMA. 1985; 253: 1590-1591.
4. National Study Commission on Cytotoxic Exposure - Recommendations for Handling Cytotoxic Agents. 1987. Available from Louis P. Jeffrey, Sc.D., Chairman, National Study Commission on Cytotoxic Exposure, Massachusetts College of Pharmacy and Allied Health Sciences, 179 Longwood Avenue, Boston, MA 02115.
5. Clinical Oncological Society of Australia: Guidelines and Recommendations for Safe Handling of Antineoplastic Agents. Med J Australia. 1983; 1:426-428.
6. Jones RB, Frank R, Mass T. Safe Handling of Chemotherapeutic Agents: A Report from the Mount Sinai Medical Center. CA Cancer J Clin. 1983; 33: 258-263.
7. American Society of Hospital Pharmacists. ASHP Technical Assistance Bulletin on Handling Cytotoxic and Hazardous Drugs. Am J Hosp Pharm. 1990; 47:1033-1049.
8. Controlling Occupational Exposure to Hazardous Drugs (OSHA Work-Practice Guidelines). Am J Health-Syst Pharm. 1996; 53: 1669-1685.

meitheal®

Mfd. for Meitheal Pharmaceuticals

Chicago, IL 60631 (USA)
©2024 Meitheal Pharmaceuticals Inc.

Mfd. by Kindos Pharmaceuticals Co., Ltd.
Chengdu, China 611731

November 2024

LB-780-V1

PRINCIPAL DISPLAY PANEL - Idarubicin Hydrochloride Injection, USP 5 mg per 5 mL Container Label

NDC 71288-184-05

Rx only

Idarubicin Hydrochloride Injection, USP

5 mg per 5 mL

(1 mg per mL)

5 mL Single-Dose Vial

FOR INTRAVENOUS USE ONLY

Sterile, Isotonic Solution

PRINCIPAL DISPLAY PANEL - Idarubicin Hydrochloride Injection, USP 5 mg per 5 mL Carton

NDC 71288-184-05

Rx only

Idarubicin Hydrochloride Injection, USP

5 mg per 5 mL

(1 mg per mL)

1 x 5 mL Single-Dose Vial

Caution: Cytotoxic Agent

FOR INTRAVENOUS USE ONLY

Sterile, Isotonic Solution

PRINCIPAL DISPLAY PANEL - Idarubicin Hydrochloride Injection, USP 10 mg per 10 mL Container Label

NDC 71288-185-10

Rx only

Idarubicin Hydrochloride Injection, USP

10 mg per 10 mL

(1 mg per mL)

10 mL Single-Dose Vial

FOR INTRAVENOUS USE ONLY

Sterile, Isotonic Solution

PRINCIPAL DISPLAY PANEL - Idarubicin Hydrochloride Injection, USP 10 mg per 10 mL Carton

NDC 71288-185-10

Rx only

Idarubicin Hydrochloride Injection, USP

10 mg per 10 mL

(1 mg per mL)

1x 10 mL Single-Dose Vial

Caution: Cytotoxic Agent

FOR INTRAVENOUS USE ONLY

Sterile, Isotonic Solution

PRINCIPAL DISPLAY PANEL - Idarubicin Hydrochloride Injection, USP 20 mg per 20 mL Container Label

NDC 71288-186-20

Rx only

Idarubicin Hydrochloride Injection, USP

20 mg per 20 mL

(1 mg per mL)

20 mL Single-Dose Vial

FOR INTRAVENOUS USE ONLY

Sterile, Isotonic Solution

PRINCIPAL DISPLAY PANEL - Idarubicin Hydrochloride Injection, USP 20 mg per 20 mL Carton

NDC 71288-186-20

Rx only

Idarubicin Hydrochloride Injection, USP

20 mg per 20 mL

(1 mg per mL)

1 x 20 mL Single-Dose Vial

Caution: Cytotoxic Agent

FOR INTRAVENOUS USE ONLY

Sterile, Isotonic Solution